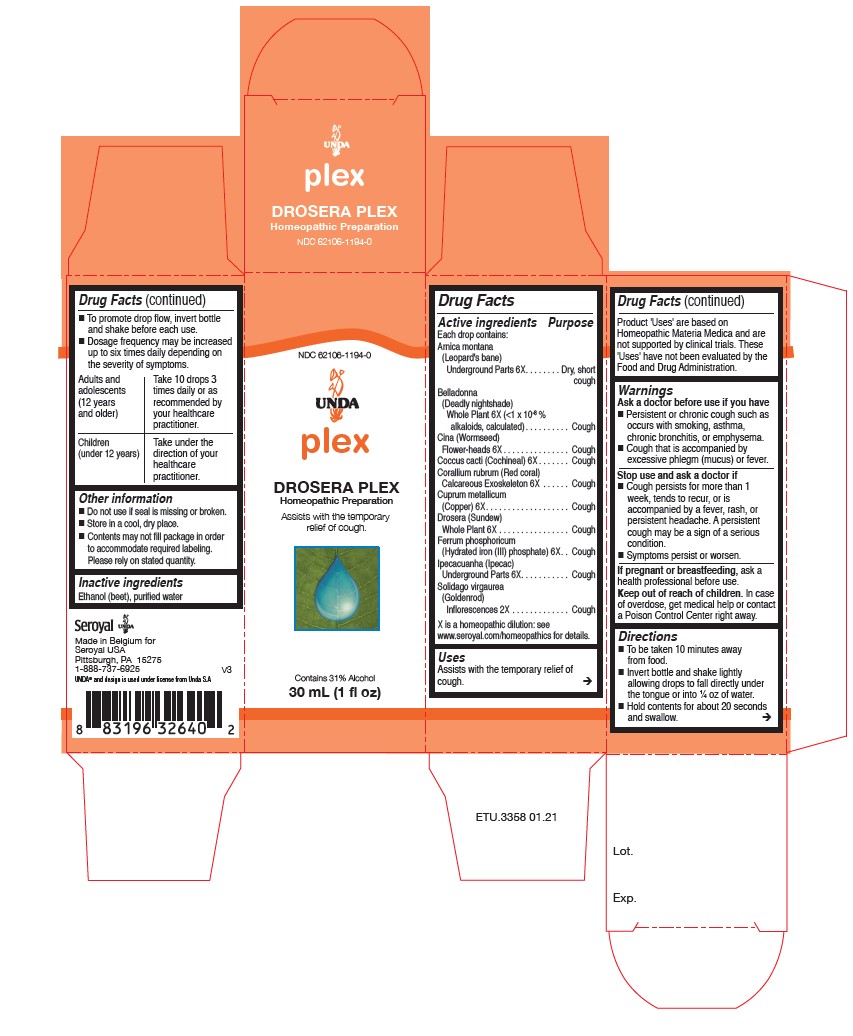 DRUG LABEL: Drosera Plex
NDC: 62106-1194 | Form: LIQUID
Manufacturer: Seroyal USA
Category: homeopathic | Type: HUMAN OTC DRUG LABEL
Date: 20210715

ACTIVE INGREDIENTS: COPPER 6 [hp_X]/30 mL; ARTEMISIA CINA FLOWER 6 [hp_X]/30 mL; FERRUM PHOSPHORICUM 6 [hp_X]/30 mL; IPECAC 6 [hp_X]/30 mL; SOLIDAGO VIRGAUREA FLOWERING TOP 2 [hp_X]/30 mL; DROSERA ROTUNDIFOLIA FLOWERING TOP 6 [hp_X]/30 mL; ATROPA BELLADONNA WHOLE 6 [hp_X]/30 mL; ARNICA MONTANA ROOT 6 [hp_X]/30 mL; PROTORTONIA CACTI 6 [hp_X]/30 mL; CORALLIUM RUBRUM EXOSKELETON 6 [hp_X]/30 mL
INACTIVE INGREDIENTS: ALCOHOL; WATER

Drosera Plex

Active ingredients
Each drop contains:

Arnica montana (Leopard's bane) Underground Parts 6X
Belladonna (Deadly nightshade) Whole Plant 6X (<1 x 10-8 % alkaloids, calculated)
Cina (Wormseed) Flower-heads 6X
Coccus cacti (Cochineal) 6X
Corallium rubrum (Red coral) Calcareous Exoskeleton 6X
Cuprum metallicum (Copper) 6X
Drosera (Sundew) Whole Plant 6X
Ferrum phosphoricum (Hydrated iron (III) phosphate) 6X
Ipecacuanha (Ipecac) Underground Parts 6X
Solidago virgaurea (Goldenrod) Inflorescences 2X

Uses
Assists with the temporary relief of cough.

Warnings
Ask a doctor before use if you have

Persistent or chronic cough such as occurs with smoking, asthma, chronic bronchitis, or emphysema.

Cough that is accompanied by excessive phlegm (mucus) or fever.

Stop use and ask a doctor if

Cough persists for more than 1 week, tends to recur, or is accompanied by a fever, rash, or persistent headache. A persistent cough may be a sign of a serious condition.

Symptoms persist or worsen.

If pregnant or breastfeeding, ask a health professional before use.
Keep out of reach of children. In case of overdose, get medical help or contact a Poison Control Center right away.

Keep out of reach of children. In case of overdose, get medical help or contact a Poison Control Center right away.

PREGNANCY OR BREAST FEEDING

If pregnant or breastfeeding, ask a health professional before use.

Other information
Do not use if seal is missing or broken.
Store in a cool, dry place.

Contents may not fill package in order to accommodate required labeling. Please rely on stated quantity.

Inactive ingredients
Ethanol (beet), purified water

Directions
To be taken ten minutes away from food.
Invert bottle and shake lightly allowing drops to fall directly under the tongue or into ¼ oz of water.
Hold contents for about 20 seconds and swallow.

To promote drop flow, invert bottle and shake before each use.
Dosage frequency may be increased up to six times daily depending on the severity of symptoms.

Adults and adolescents (12 years and older)

Take 10 drops three times daily or as recommended by your healthcare practitioner.
Children (under 12 years)

Take under the direction of your healthcare practitioner.

Uses
Assists with the temporary relief of cough.

Directions
To be taken ten minutes away from food.
Invert bottle and shake lightly allowing drops to fall directly under the tongue or into ¼ oz of water.
Hold contents for about 20 seconds and swallow.

To promote drop flow, invert bottle and shake before each use.
Dosage frequency may be increased up to six times daily depending on the severity of symptoms.

Adults and adolescents (12 years and older)

Take 10 drops three times daily or as recommended by your healthcare practitioner.
Children (under 12 years)

Take under the direction of your healthcare practitioner.

PACKAGE LABEL

NDC 62106-1194-0

UNDA

plex

DROSERA PLEX

Homeopathic Preparation

Assists with the temporary relief of cough.

Contains 31% Alcohol

1 fl oz (30 mL)